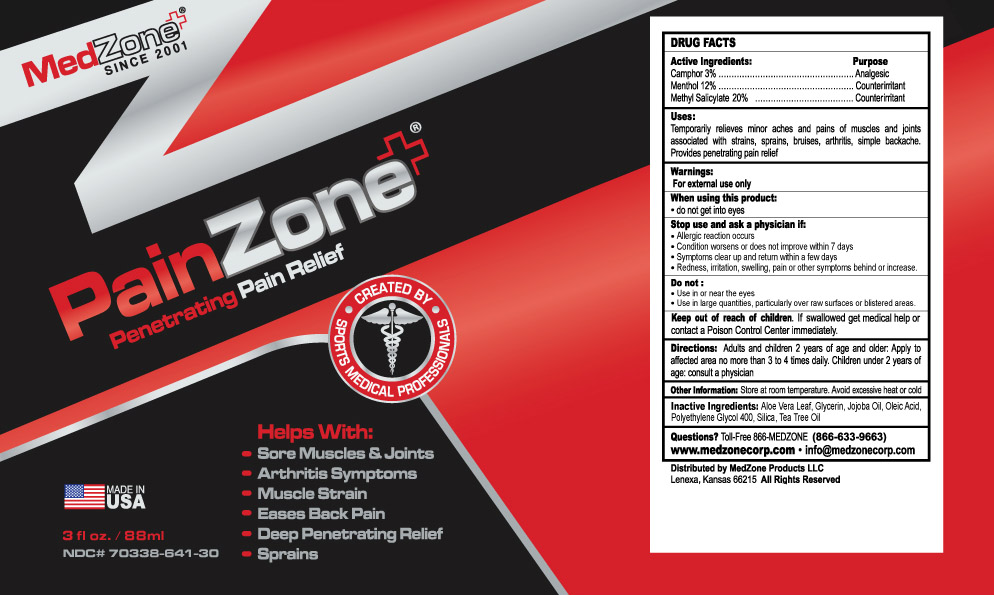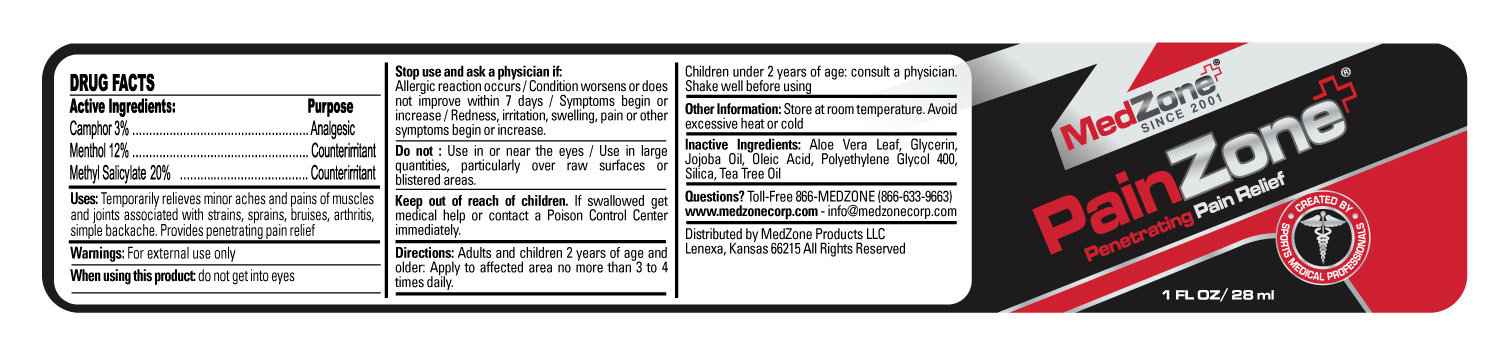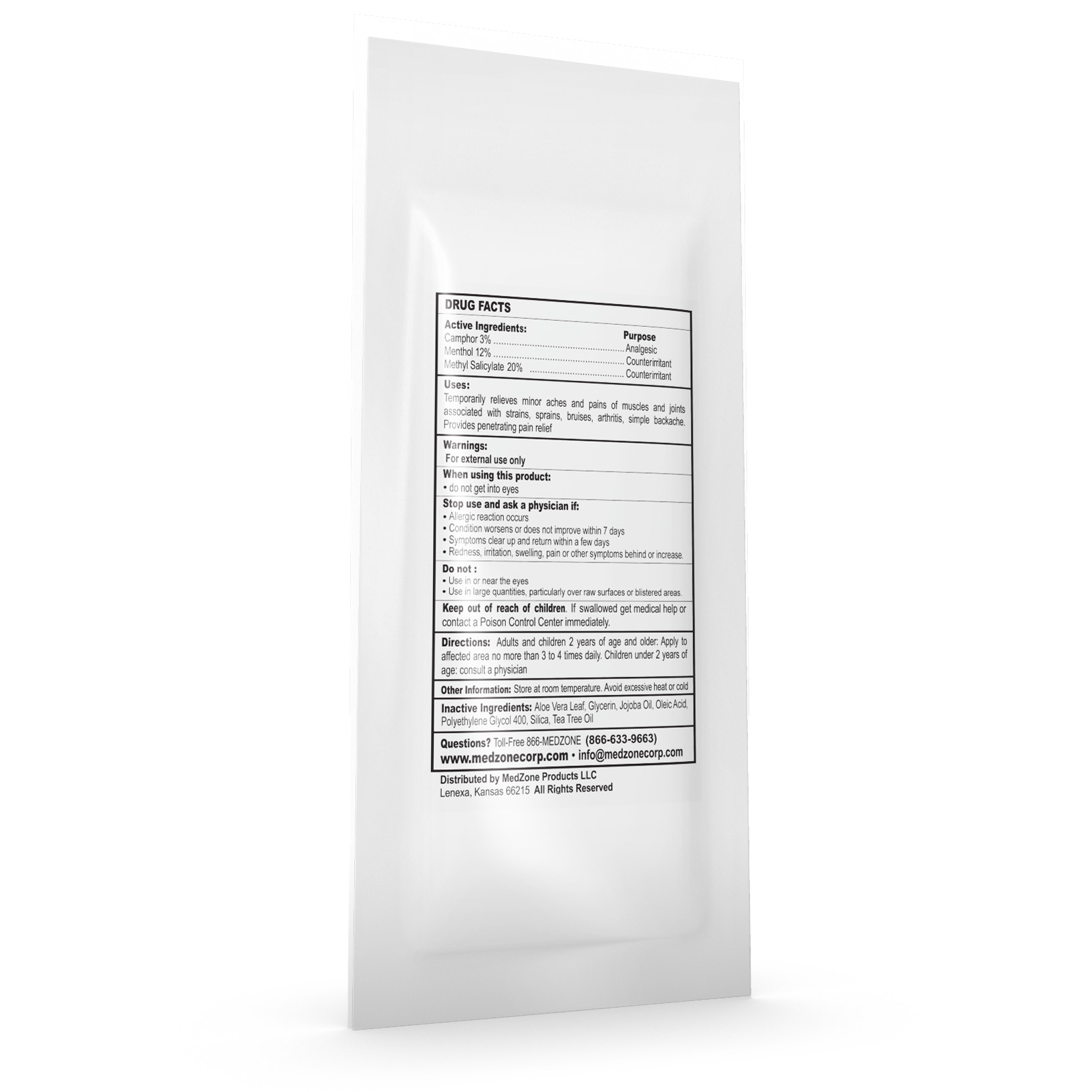 DRUG LABEL: PainZone
NDC: 70338-641 | Form: CREAM
Manufacturer: MedZone Products LLC
Category: otc | Type: HUMAN OTC DRUG LABEL
Date: 20180212

ACTIVE INGREDIENTS: CAMPHOR, (-)- 30 mg/1 g; MENTHOL 120 mg/1 g; METHYL SALICYLATE 200 mg/1 g
INACTIVE INGREDIENTS: ALOE VERA LEAF; GLYCERIN; JOJOBA OIL; OLEIC ACID; POLYETHYLENE GLYCOL 400; SILICON DIOXIDE; TEA TREE OIL

PainZone

Active Ingredients

Camphor 3%

Menthol 12%

Methyl Salicylate 20%

Purpose

Analgesic

Counterirritant

Counterirritant

Uses

Temporarily relieves minor aches and pains of muscle and joints associated with strains, sprains, arthritis, simple backache.

Provides pentrating pain relief.

Warnings

For external use only.

When using this product

- do not get into eyes

Stop use and ask a physician if

- Allergic reaction occurs
- Condition worsens or does not improve within 7 days
- Symptoms clear up and return within a few days
- Redness, irritation, swelling, pain or other symptoms begin or increase

Do not

- Use in or near the eyes
- Use in large quantities, particularly over raw surfaces or blistered areas

Keep out of reach of children

If swallowed get medical help or contact a Poison Control Center immediately.

Directions

Adults and children 2 years of age and older: Apply to affected area no more than 3 to 4 times daily. Children under 2 years of age: consult a physician.

Other Information

Store at room temperature. Avoid excessive heat or cold.

Inactive Ingredients

Aloe Vera Leaf, Glycerin, Jojoba Oil, Oleic Acid, Polyethylene Glycol 400, Silica, Tea Tree Oil

Questions?

Toll-Free 866-MEDZONE (866-633-9663)

www.medzonecorp.com info@medzonecorp.com

HOW SUPPLIED

Distributed by MedZone Products LLC

Lenexa, Kansas 66215 All Rights Reserved